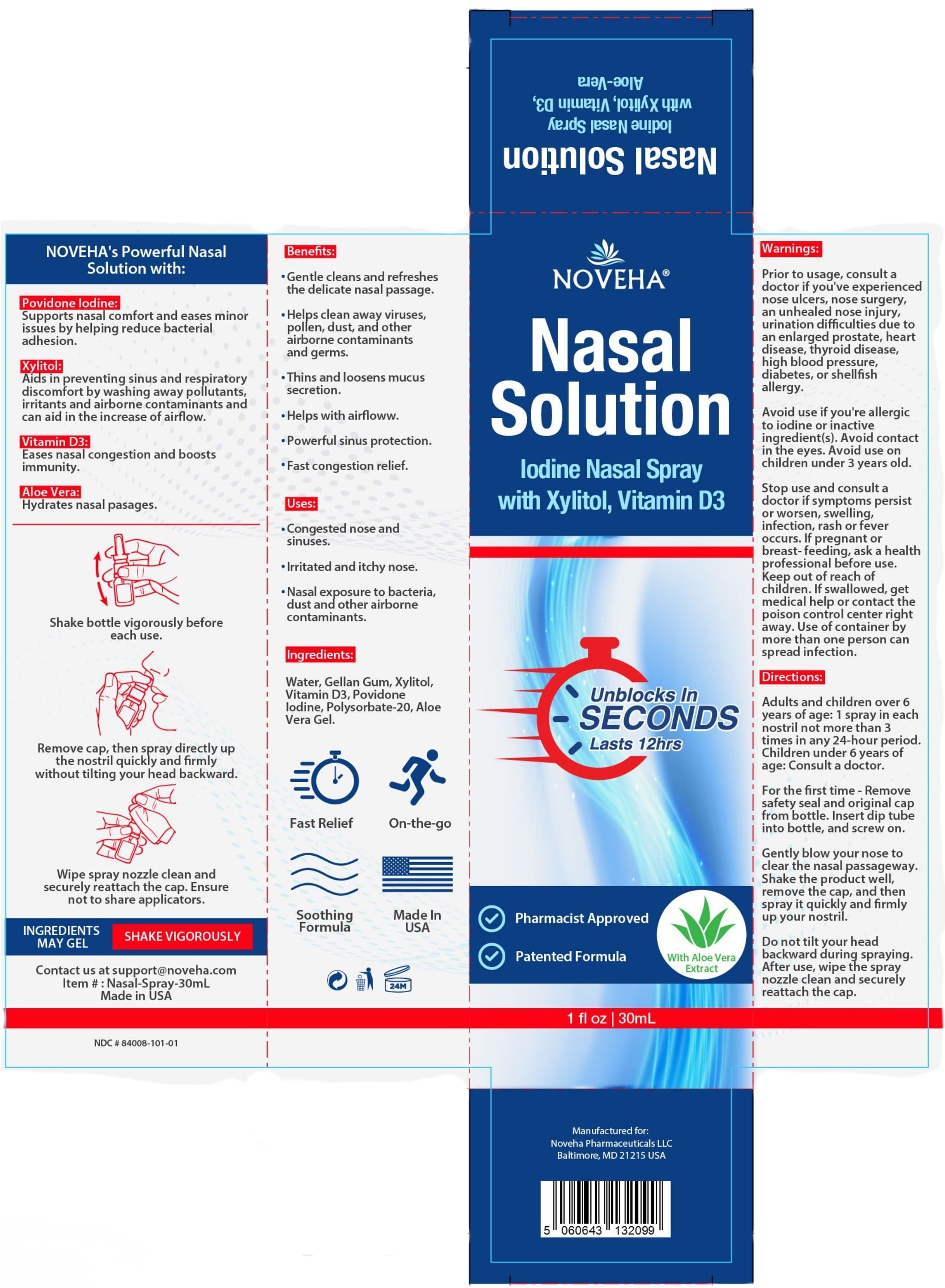 DRUG LABEL: Nasal Solution
NDC: 84008-101 | Form: LIQUID
Manufacturer: Bullet Point LLC
Category: otc | Type: HUMAN OTC DRUG LABEL
Date: 20260101

ACTIVE INGREDIENTS: POVIDONE-IODINE 1 g/100 mL
INACTIVE INGREDIENTS: ALOE VERA LEAF; XYLITOL; CHOLECALCIFEROL; WATER; GELLAN GUM (LOW ACYL); CARRAGEENAN; POLYSORBATE 20; SODIUM HYDROXIDE

Nasal Solution

ACTIVE INGREDIENT

Povidone-lodine 1%

INACTIVE INGREDIENT

Purifed water,xylitol, vitamin D3,polysorbate, gellangum, carrageenan, sodiumhydroxide, aloe vera.

PURPOSE

*Gently washes and soothesthe delicate nasal passage.
*Helps clean away viruses,pollen, dust, and otherairborne contaminantsand germs.
Thins and loosens mucussecretion.
*Aids in improving airflow.
*Powerful sinus protection.
*Fast congestion relief.

Uses:
*Congested nose andsinuses.
*lrritated and itchy nose.
*Nasal exposure to bacteria,dust and other airbornecontaminants.

DO NOT USE

Avoid use if you're allergicto iodine or inactive ingredient(s).Avoid contactin the eyes. Avoid use onchildren under 3 years old.

Stop use and consult adoctor if symptoms persistor worsen, swelling,infection, rash or feveroccurs.lf pregnant orbreast- feeding, ask a health professional before use.

KEEP OUT OF REACH OF CHILDREN

Keep out of reach ofchildren. lf swallowed, getmedical help or contact the poison control center rightaway.

PREGNANCY OR BREAST FEEDING

lf pregnant orbreast- feeding, ask a health professional before use.

WARNINGS

Use of container bymore than one person canspread infection.

Directions:
Adults and children over 6years of age: 1 spray in eachnostril not more than 3times in any 24-hour period,Children under é years ofage: Consult a doctor.
For the frst time -Removesafety seal and original capfrom bottle. insert dip tubeinto bottle, and screw on.
Gently blow your nose toclear the nasal passageway.Shake the product well,remove the cap, and thenspray it quickly and frmlyup your nostril.
Do not tilt your headbackward during sprayingAfter use, wipe the spraynozzle clean and securelyreattach the cap.

QUESTIONS

You can email us at support@noveha.com.com for more help!